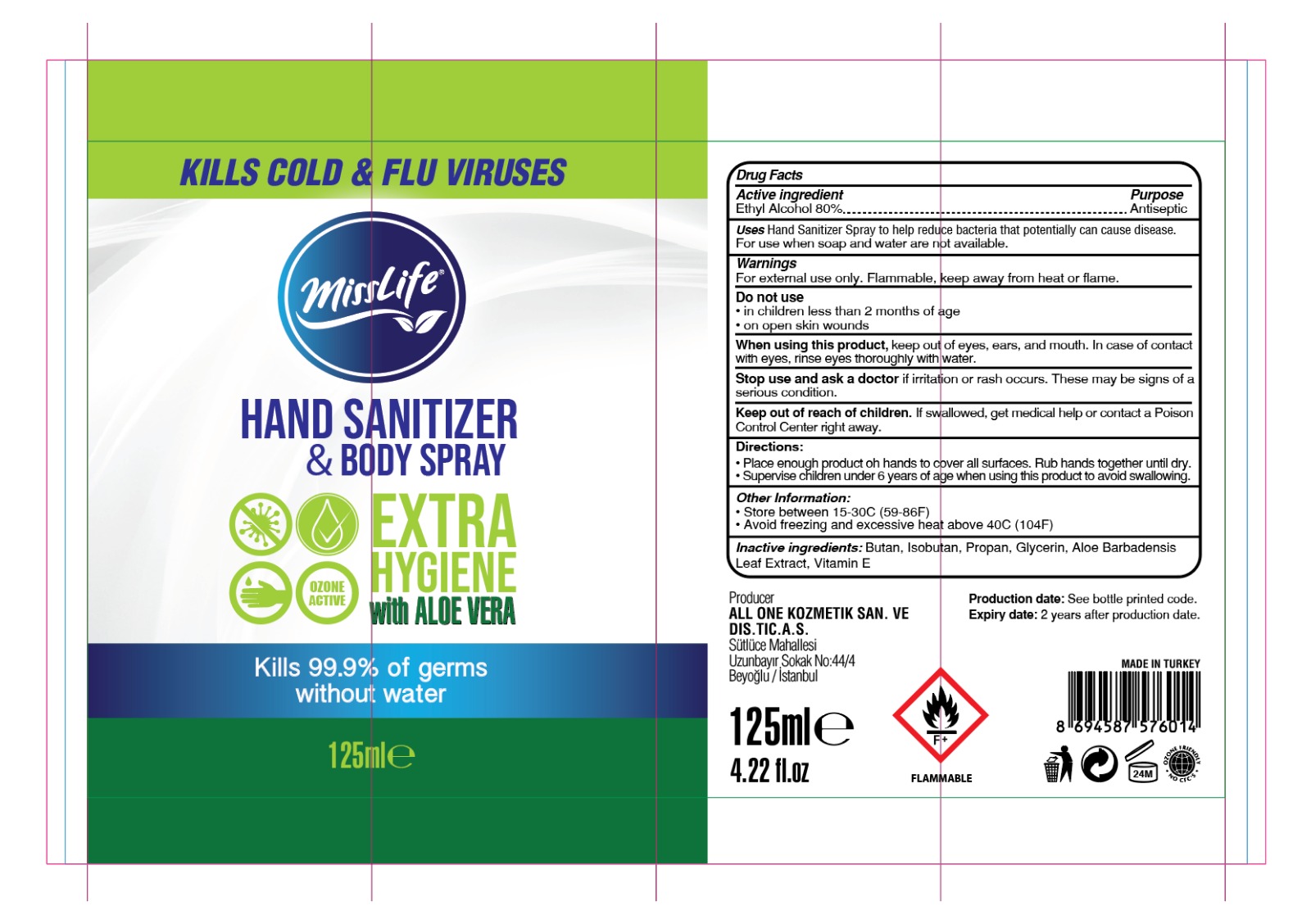 DRUG LABEL: MISS LIFE HAND SANITIZER WITH ALOE VERA
NDC: 75348-999 | Form: SPRAY
Manufacturer: ALL ONE KOZMETIK SANAYI DIS TICARET ANONIM SIRKETI
Category: otc | Type: HUMAN OTC DRUG LABEL
Date: 20200612

ACTIVE INGREDIENTS: ALCOHOL 80 mL/100 mL
INACTIVE INGREDIENTS: ISOBUTANE; BUTANE; .ALPHA.-TOCOPHEROL; ALOE VERA LEAF; PROPANE; GLYCERIN

Hand Sanitizer

DESCRIPTION

MISS LIFE HAND SANITIZER & BODY SPRAY

Active Ingredient(s)

Ethyl Alcohol 80%. Purpose: Antiseptic

Purpose

Antiseptic

Use

Hand Sanitizer Spray to help reduce bacteria that potentially can cause disease. For use when soap and water are not available.

Warnings

For external use only. Flammable. Keep away from heat or flame

Do not use

- in children less than 2 months of age
- on open skin wounds

When using this product keep out of eyes, ears, and mouth. In case of contact with eyes, rinse eyes thoroughly with water.

Stop use and ask a doctor if irritation or rash occurs. These may be signs of a serious condition.

Keep out of reach of children. If swallowed, get medical help or contact a Poison Control Center right away.

Directions

- Place enough product on hands to cover all surfaces. Rub hands together until dry.
- Supervise children under 6 years of age when using this product to avoid swallowing.

Other information

- Store between 15-30C (59-86F)
- Avoid freezing and excessive heat above 40C (104F)

Inactive ingredients

Butan, Isobutan, Propan, Glycerol (Glycerin, Glycerine), Vitamin E, Panthenol

Package Label - Principal Display Panel

Producer

ALL ONE KOZMETIK SAN. VE DIS. TIC. A. S.

Sutluce Mahallesi

Uzunbayır Sokak No:44/4

Beyoglu/Istanbul

4.22 fl. oz.

FLAMMABLE

Production date: See bottle printed code.

Expiry date: 2 years after production date.

MADE IN TURKEY

KILLS COLD & FLU VIRUSES

with ALOE VERA

Kills 99.9% of germs without water

EXTRA HYGIENE